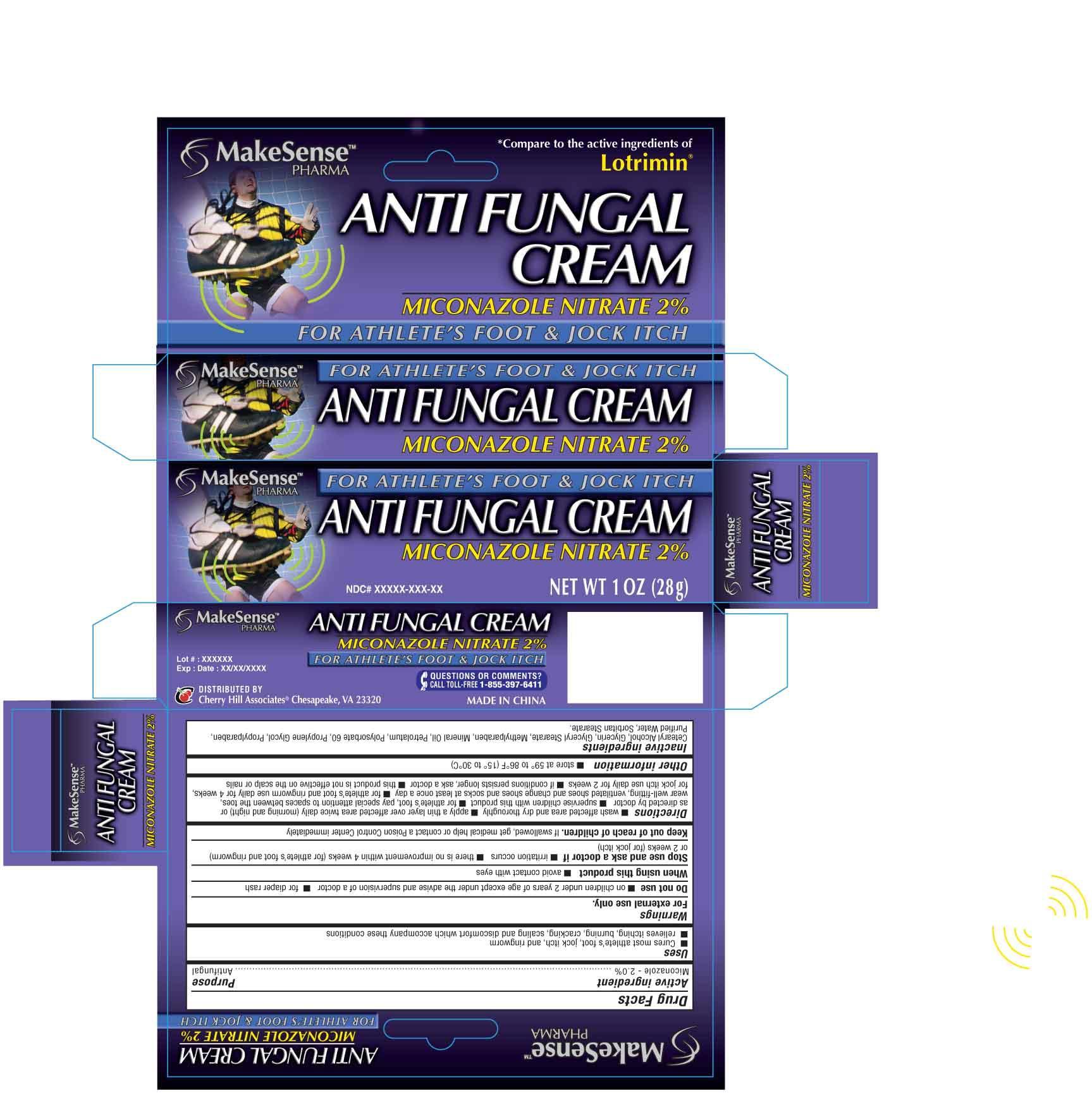 DRUG LABEL: MakeSense
NDC: 69020-208 | Form: CREAM
Manufacturer: Cherry Hill Sales Co
Category: otc | Type: HUMAN OTC DRUG LABEL
Date: 20140731

ACTIVE INGREDIENTS: MICONAZOLE NITRATE 2 g/100 g
INACTIVE INGREDIENTS: CETOSTEARYL ALCOHOL; GLYCERIN; GLYCERYL STEARATE SE; METHYLPARABEN; MINERAL OIL; PETROLATUM; POLYSORBATE 60; PROPYLENE GLYCOL; PROPYLPARABEN; SORBITAN MONOSTEARATE; WATER

Drug Facts

Active Ingredient

Miconazole 2.0%

Purpose

Antifungal

Uses

■ Cures most athlete's foot, jock itch, and ringworm

■ relieves itching, burning, cracking, scaling and discomfort which accompany these conditions

Warnings

For external use only.

Do not use

■ on children under 2 years of age except under the advise and supervision of a doctor ■ for diaper rash

When using this product

■ avoid contact with eyes

Stop use and ask a doctor if

■ irritation occurs ■ there is no improvement within 4 weeks (for athlete's foot and ringworm) or 2 weeks (jock itch)

Keep out of reach of children

If swallowed, get medical help or contact a Poison Control Center immediately

Directions

■ wash affected area and dry thoroughly ■ apply a thin layer over affected area twice daily (morning and night) or as directed by a doctor ■ supervise children in the use of this product ■ for athlete's foot, pay special attention to spaces between the toes, wear well-fitting, ventilated shoes and change shoes and socks at least once a day ■ for athlete's foot and ringworm use daily for 4 weeks, for jock itch use daily for 2 weeks ■ if conditions persist longer, ask a doctor ■ this product is not effective on the scalp or nails.

Other Information

■ store at 59 to 86F (15 to 30C)

Inactive Ingredients

Cetearyl Alcohol, Glycerin, Glyceryl Stearate, Methylparaben, Mineral Oil, Petrolatum, Polysorbate 60, Propylene Glycol, Propylparaben, Purified Water, Sorbitan Stearate